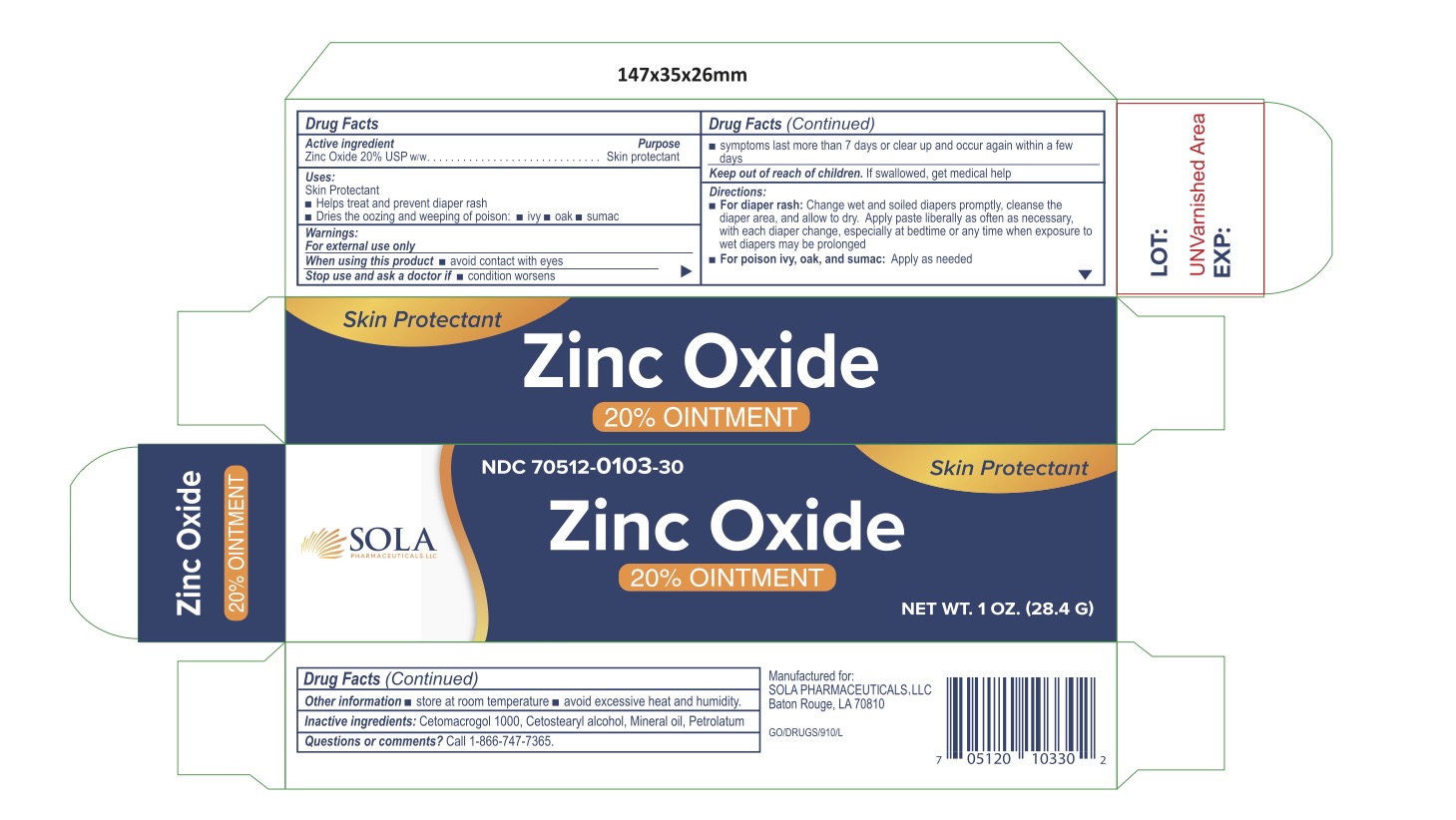 DRUG LABEL: Zinc Oxide 20%
NDC: 70512-103 | Form: OINTMENT
Manufacturer: SOLA Pharmaceuticals
Category: otc | Type: HUMAN OTC DRUG LABEL
Date: 20220705

ACTIVE INGREDIENTS: ZINC OXIDE 200 mg/1 g
INACTIVE INGREDIENTS: CETETH-20; PETROLATUM; CETOSTEARYL ALCOHOL; MINERAL OIL

Zinc Oxide 20% Ointment

Active Ingredient

Zinc Oxide 20%

Purpose

Skin protectant

Uses

Skin Protectant

- Helps treat and prevent diaper rash
- Dries the ozzing and weeping of poison: •Ivy •Oak •Sumac

Warnings

For external use only

When using this product

- avoid contact with eyes

Stop use and ask a doctor if

- condition worsens
- symptoms last more than 7 days or clear up and occur again within a few days

Keep out of reach of children. If swallowed, get medical help

Directions

- For diaper rash: Change wet and soiled diapers promptly, cleanse the diaper area, and allow to dry. Apply paste liberally as often as necessary, with each diaper change, especially at bedtime or any time when exposure to wet diapers may be prolonged
- For poison ivy, oak, and sumac: Apply as needed

Other Information

- Store at room temperature
- Avoid excessive heat and humidity

Inactive ingredients

Cetomacrogol 1000, Cetostearyl alcohol, Mineral oil, Petrolatum

PACKAGE LABEL

Questions of comments? Call 1-866-747-7365

Manufactured for : SOLA Pharmaceuticals
Baton Rouge, LA 70810

Store at room temperature. Avoid excessive heat and humidity.

Zinc Oxide 20% Ointment
NDC 70512-103-30

Qty: 28.4g